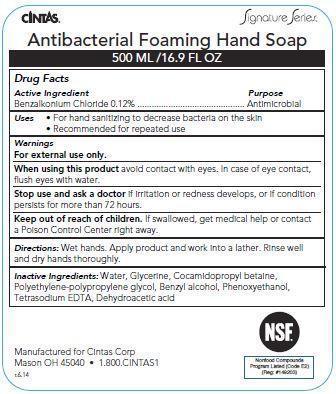 DRUG LABEL: Signature Antibacterial Foaming Hand
                
NDC: 42961-011 | Form: LIQUID
Manufacturer: Cintas Corp.
Category: otc | Type: HUMAN OTC DRUG LABEL
Date: 20150331

ACTIVE INGREDIENTS: BENZALKONIUM CHLORIDE 1.2 mg/1 mL
INACTIVE INGREDIENTS: WATER; GLYCERIN; COCAMIDOPROPYL BETAINE; POLYETHYLENE GLYCOLS; BENZYL ALCOHOL; PHENOXYETHANOL; EDETATE SODIUM; DEHYDROACETIC ACID

Drug Facts

Active Ingredient

Benzalkonium Chloride 0.12%

Purpose

Antimicrobial

Uses

For hand sanitizing to decrease bacteria on skin

Recommended for repeated use

Warnings

For external use only.

When using this product avoid contact with eyes. In case of eye contact, flush eyes with water.

Stop use and ask a doctor if irritation or redness develops, or if condition persists for more than 72 hours.

Keep out of reach of children. If swallowed, get medical help or contact a Poison Control Center right away.

Directions:

Wet hands.

Apply product and work into a lather.

Rinse well and dry hands thoroughly.

Inactive Ingredients:

Water, Glycerine, Cocamidopropyl betaine, Polyethylene-polypropylene glycol, Benzyl alcohol, Phenoxyethanol, Tetrasodium EDTA, Dehydroacetic acid

PACKAGE LABEL

Cintas

Signature Series

Antibacterial Foaming Hand Soap

500 ML/16.9 FL OZ